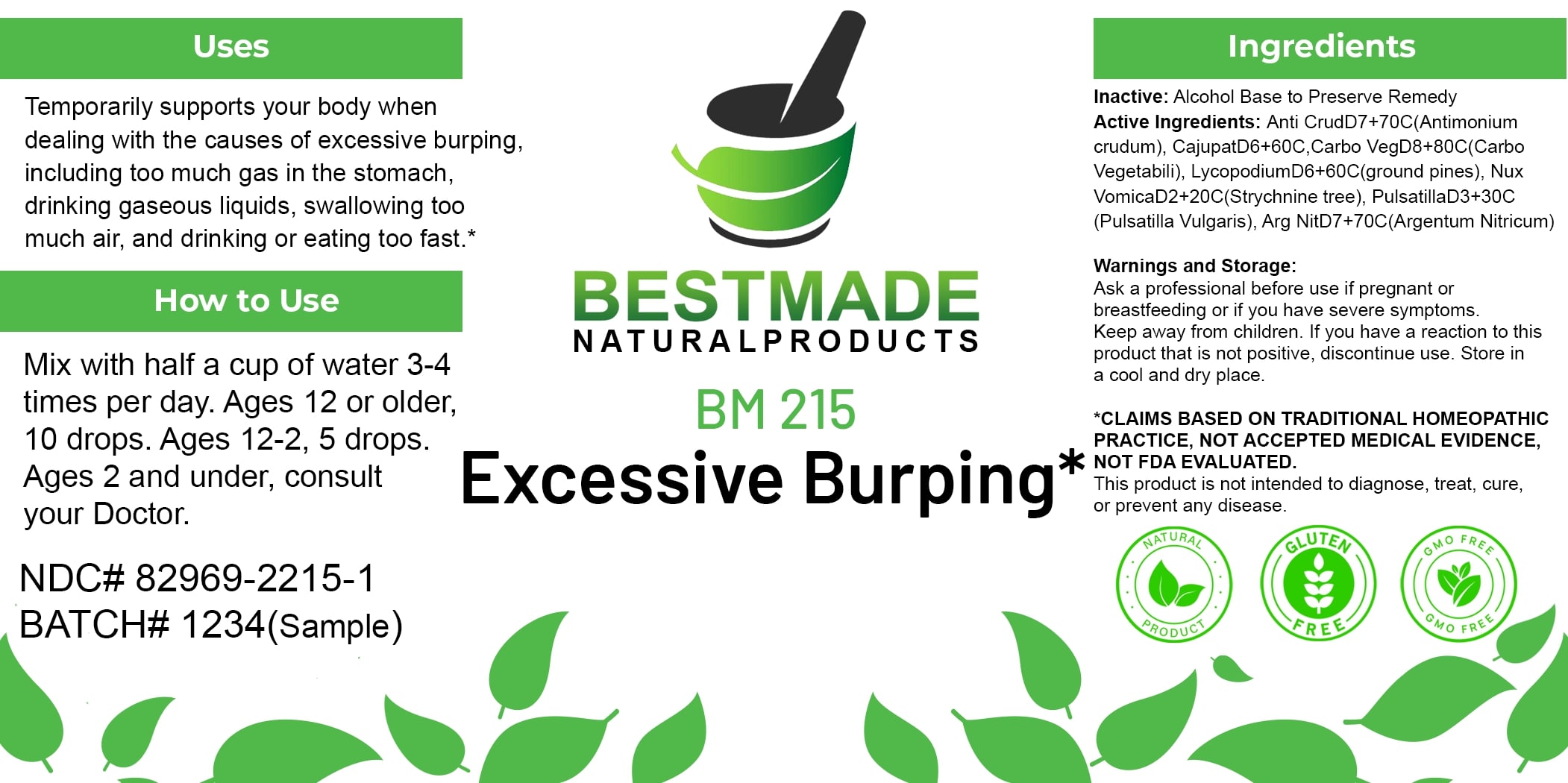 DRUG LABEL: Bestmade Natural Products BM215
NDC: 82969-2215 | Form: LIQUID
Manufacturer: Bestmade Natural Products
Category: homeopathic | Type: HUMAN OTC DRUG LABEL
Date: 20250303

ACTIVE INGREDIENTS: ACTIVATED CHARCOAL 30 [hp_C]/30 [hp_C]; STRYCHNOS NUX-VOMICA SEED 30 [hp_C]/30 [hp_C]; ANTIMONY TRISULFIDE 30 [hp_C]/30 [hp_C]; CAJUPUT OIL 30 [hp_C]/30 [hp_C]; LYCOPODIUM CLAVATUM SPORE 30 [hp_C]/30 [hp_C]; PULSATILLA VULGARIS 30 [hp_C]/30 [hp_C]; SILVER NITRATE 30 [hp_C]/30 [hp_C]
INACTIVE INGREDIENTS: ALCOHOL 30 [hp_C]/30 [hp_C]

BM215

DOSAGE AND ADMINISTRATION

How to Use

Mix with half a cup of water 3-4 times per day. Ages 12 or older, 10 drops. Ages 12-2, 5 drops. Ages 2 and under, consult your Doctor.

Uses

Temporarily supports your body when dealing with the causes of excessive burping, including too much gas in the stomach, drinking gaseous liquids, swallowing too much air, and drinking or eating too fast.*

*CLAIMS BASED ON TRADITIONAL HOMEOPATHIC PRACTICE, NOT ACCEPTED MEDICAL EVIDENCE. NOT FDA EVALUATED.

This product is not intended to diagnose, treat, cure, or prevent any disease.

INACTIVE INGREDIENT

Ingredients

Inactive: Alcohol Base to Preserve Remedy

ACTIVE INGREDIENT

Active Ingredients: Anti CrudD7+70C(Antimonium crudum), CajupatD6+60C, Carbo VegD6+60C(Carbo Vegetabilis), LycopodiumD6+60C(Ground pines), Nux VomicaD2+20C(Strychnine tree), PulsatillaD3+30C (Pulsatilla Vulgaris), Arg NitD7+70C(Argentum Nitricum)

KEEP OUT OF REACH OF CHILDREN

Warnings and Storage:

Ask a professional before use if pregnant or breastfeeding or if you have severe symptoms. Keep away from children. If you have a reaction to this product that is not positive, discontinue use. Store in a cool and dry place.

Warnings and Storage:

Ask a professional before use if pregnant or breastfeeding or if you have severe symptoms. Keep away from children. If you have a reaction to this product that is not positive, discontinue use. Store in a cool and dry place.

*CLAIMS BASED ON TRADITIONAL HOMEOPATHIC PRACTICE, NOT ACCEPTED MEDICAL EVIDENCE. NOT FDA EVALUATED.

This product is not intended to diagnose, treat, cure, or prevent any disease.

Uses

Temporarily supports your body when dealing with the causes of excessive burping, including too much gas in the stomach, drinking gaseous liquids, swallowing too much air, and drinking or eating too fast.*

*CLAIMS BASED ON TRADITIONAL HOMEOPATHIC PRACTICE, NOT ACCEPTED MEDICAL EVIDENCE. NOT FDA EVALUATED.

This product is not intended to diagnose, treat, cure, or prevent any disease.

Entire package label